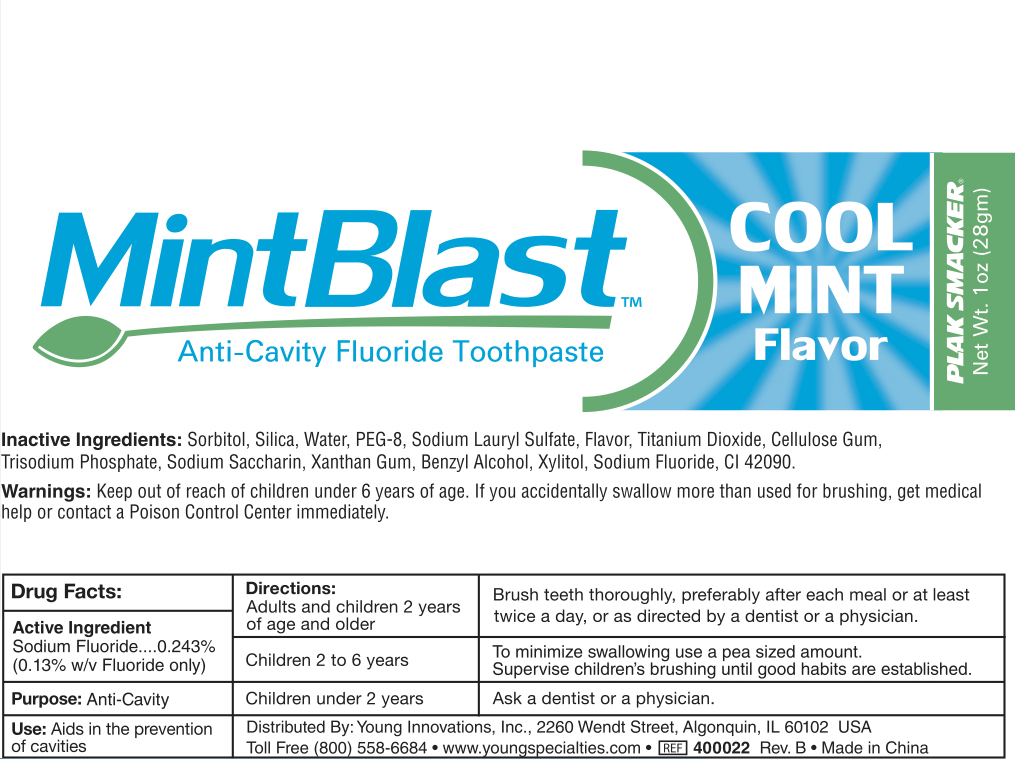 DRUG LABEL: Plak Smacker
NDC: 71775-080 | Form: PASTE
Manufacturer: LMZ
Category: otc | Type: HUMAN OTC DRUG LABEL
Date: 20210318

ACTIVE INGREDIENTS: SODIUM FLUORIDE 130 mg/100 g
INACTIVE INGREDIENTS: POLYETHYLENE GLYCOL 400; BENZYL ALCOHOL; XYLITOL; SODIUM PHOSPHATE, TRIBASIC, ANHYDROUS; CARBOXYMETHYLCELLULOSE; SACCHARIN SODIUM; SORBITOL; SILICON DIOXIDE; WATER; SODIUM LAURYL SULFATE; TITANIUM DIOXIDE; XANTHAN GUM; FD&C BLUE NO. 1

Mint Blast Toothpaste

Active Ingredients

Sodium Fluoride 0.243% (equivalent to 0.13% w/v fluoride ion)

Purpose

Anti-cavity

Uses

Aids in the prevention of cavities

Warnings

If you accidentally swallow more than used for brushing, get medical help or contact a Poison Control Center immediately.

Keep out of reach of children under 6 years of age.

Directions

Adults and children 2 years of age and older: Brush teeth thoroughly, preferably after each meal or at least twice a day, or as directed by a dentist or a physician.

Children 2 to 6 years: To minimize swallowing use a pea sized amount. Supervise children's brushing until good habits are established.

Children under 2 years: Ask a dentist or a physician.

Inactive Ingredients

Sorbitol, Silica, Water, PEG-8, Sodium lauryl sulfate, Flavor, Titanium dioxide, Cellulose gum, Trisodium phosphate, Sodium saccharin, Xanthan gum, Benzyl alcohol, Xylitol, CI 42090

Principal Display Panel

28 g NDC: 71775-080-01